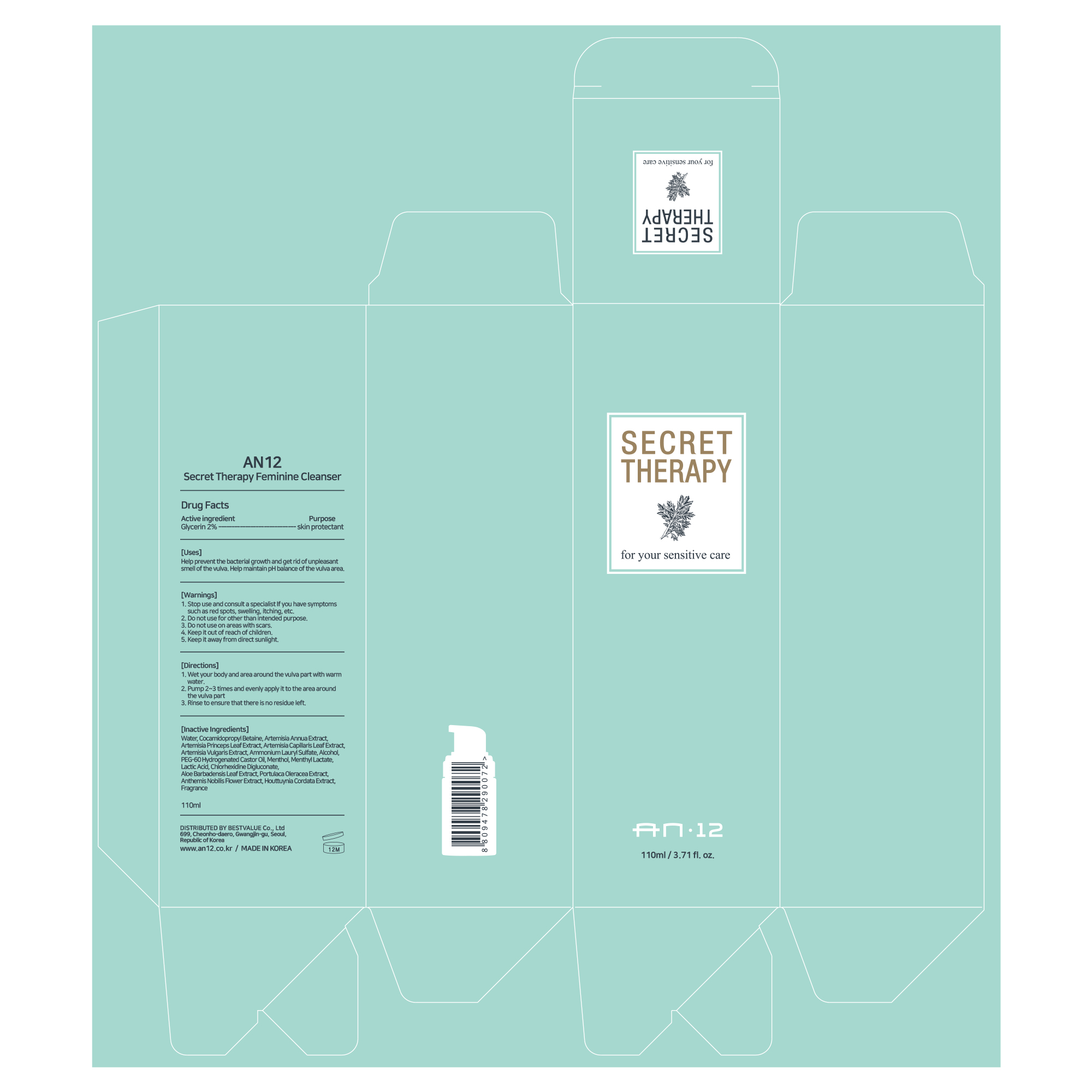 DRUG LABEL: AN12 Secret Therapy Feminine Cleanser
NDC: 82385-103 | Form: LIQUID
Manufacturer: BESTVALUE Co., Ltd
Category: otc | Type: HUMAN OTC DRUG LABEL
Date: 20250131

ACTIVE INGREDIENTS: GLYCERIN 2 g/100 mL
INACTIVE INGREDIENTS: FRAGRANCE FRESH CITRUS FLORAL ORC1501495; ARTEMISIA ANNUA FLOWERING TOP; ARTEMISIA PRINCEPS LEAF; ARTEMISIA CAPILLARIS LEAF; MENTHOL; PURSLANE; ARTEMISIA VULGARIS WHOLE; POLYOXYL 60 HYDROGENATED CASTOR OIL; HOUTTUYNIA CORDATA FLOWERING TOP; CHLORHEXIDINE GLUCONATE; ALOE VERA LEAF; CHAMAEMELUM NOBILE FLOWER; WATER; MENTHYL LACTATE, (-)-; LACTIC ACID; COCAMIDOPROPYL BETAINE; ALCOHOL; AMMONIUM LAURYL SULFATE

82385-103 AN12 Secret Therapy Feminine Cleanser

Active Ingredient

Glycerin 2%

Purpose

skin protectant

Uses

Help prevent the bacterial growth and get rid of unpleasant smell of the vulva.

Help maintain pH balance of the vulva area.

Warnings

Do not use for other than intended purpose.

Warnings

Stop use and consult a specialist If you have symptoms such as red spots, swelling, itching, etc.

Warnings

Do not use on areas with scars.

Warnings

Keep it out of reach of children.

Inactive Ingredients

Water, Cocamidopropyl Betaine, Artemisia Annua Extract, Artemisia Princeps Leaf Extract, Artemisia Capillaris Leaf Extract,

Artemisia Vulgaris Extract, Ammonium Lauryl Sulfate, Alcohol, PEG-60 Hydrogenated Castor Oil, Menthol, Menthyl Lactate,

Lactic Acid, Chlorhexidine Digluconate, Aloe Barbadensis Leaf Extract, Portulaca Oleracea Extract, Anthemis Nobilis Flower Extract, Houttuynia Cordata Extract, Fragrance

Directions

1. Wet your body and area around the vulva part with warm water.

2. Pump 2~3 times and evenly apply it to the area around the vulva part

3. Rinse to ensure that there is no residue left.